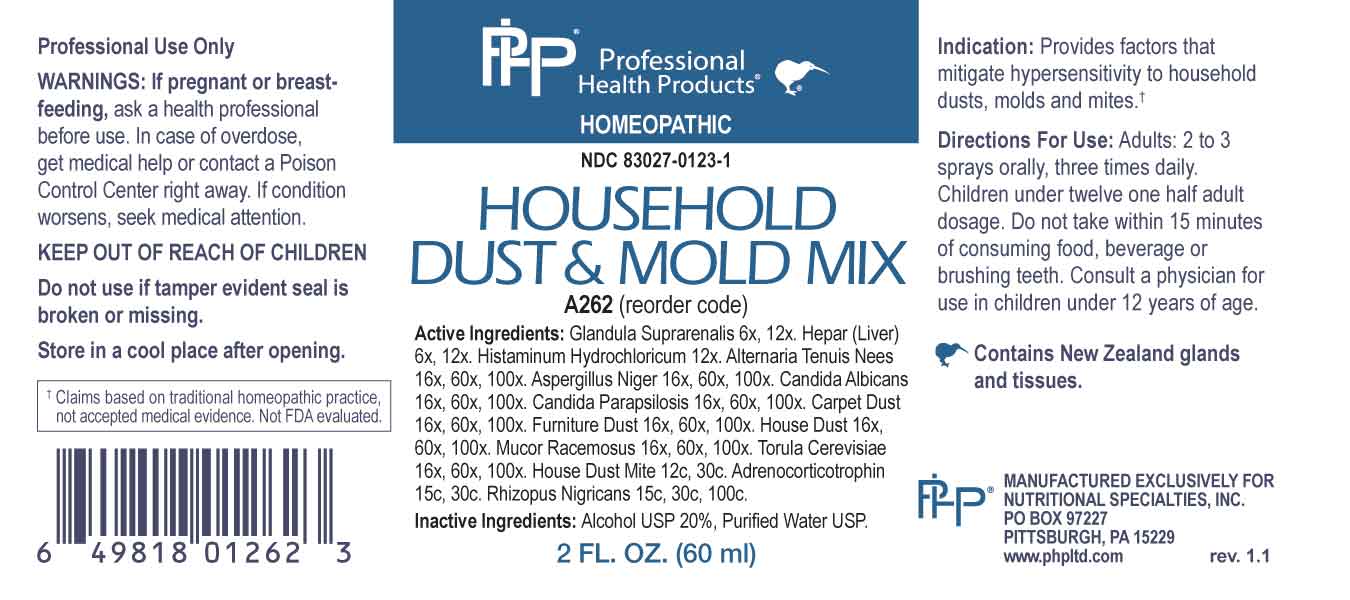 DRUG LABEL: Household Dust and Mold Mix
NDC: 83027-0123 | Form: SPRAY
Manufacturer: Nutritional Specialties, Inc.
Category: homeopathic | Type: HUMAN OTC DRUG LABEL
Date: 20250515

ACTIVE INGREDIENTS: BOS TAURUS ADRENAL GLAND 6 [hp_X]/1 mL; BEEF LIVER 6 [hp_X]/1 mL; HISTAMINE DIHYDROCHLORIDE 12 [hp_X]/1 mL; ALTERNARIA ALTERNATA 16 [hp_X]/1 mL; ASPERGILLUS NIGER VAR. NIGER 16 [hp_X]/1 mL; CANDIDA ALBICANS 16 [hp_X]/1 mL; CANDIDA PARAPSILOSIS 16 [hp_X]/1 mL; HOUSE DUST 16 [hp_X]/1 mL; MUCOR RACEMOSUS 16 [hp_X]/1 mL; SACCHAROMYCES CEREVISIAE 16 [hp_X]/1 mL; DERMATOPHAGOIDES PTERONYSSINUS 12 [hp_C]/1 mL; CORTICOTROPIN 15 [hp_C]/1 mL; RHIZOPUS STOLONIFER 15 [hp_C]/1 mL
INACTIVE INGREDIENTS: WATER; ALCOHOL

DRUG FACTS:

ACTIVE INGREDIENTS:

Glandula Suprarenalis 6X, 12X, Hepar (Liver) 6X, 12X, Histaminum Hydrochloricum 12X, Alternaria Tenuis Nees 16X, 60X, 100X, Aspergillus Niger 16X, 60X, 100X, Candida Albicans 16X, 60X, 100X, Candida Parapsilosis 16X, 60X, 100, Dust 16X, 60X, 100, Mucor Racemosus 16X, 60X, 100, Torula Cerevisiae 16X, 60X, 100X, House Dust Mite 12C, 30C, Adrenocorticotrophin 15C, 30C, Rhizopus Nigricans 15C, 30C, 100C.

PURPOSE:

Provides factors that mitigate hypersensitivity to household dusts, molds and mites.†

†Claims based on traditional homeopathic practice, not accepted medical evidence. Not FDA evaluated.

WARNINGS:

Professional Use Only

If pregnant or breast-feeding, ask a health professional before use.

In case of overdose, get medical help or contact a Poison Control Center right away.

If condition worsens, seek medical attention.

KEEP OUT OF REACH OF CHILDREN

Do not use if tamper evident seal is broken or missing.

Store in a cool place after opening

KEEP OUT OF REACH OF CHILDREN:

In case of overdose, get medical help or contact a Poison Control Center right away.

DIRECTIONS:

Adults: 2 to 3 sprays orally, three times daily. Children under twelve one half adult dosage. Do not take within 15 minutes of consuming food, beverage or brushing teeth. Consult a physician for use in children under 12 years of age.

INDICATIONS:

Provides factors that mitigate hypersensitivity to household dusts, molds and mites.†

†Claims based on traditional homeopathic practice, not accepted medical evidence. Not FDA evaluated.

INACTIVE INGREDIENTS:

Alcohol USP 20%, Purified Water USP.

QUESTIONS:

MANUFACTURED EXCLUSIVELY FOR

NUTRITIONAL SPECIALTIES, INC.

PO BOX 97227

PITTSBURG, PA 15229

www.phpltd.com

PACKAGE LABEL DISPLAY:

Professional

Health Products

HOMEOPATHIC

NDC 83027-0123-1

HOUSEHOLD

DUST & MOLD MIX

2 FL. OZ (60 ml)